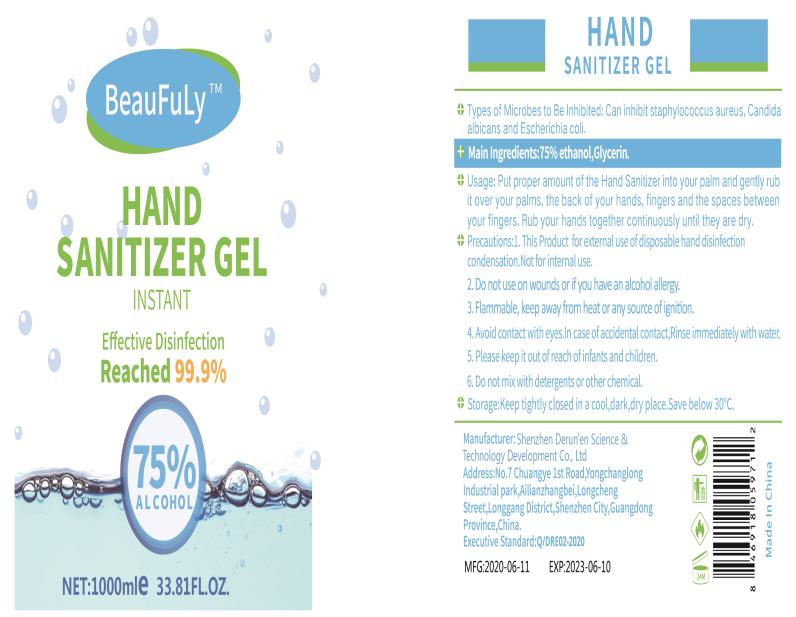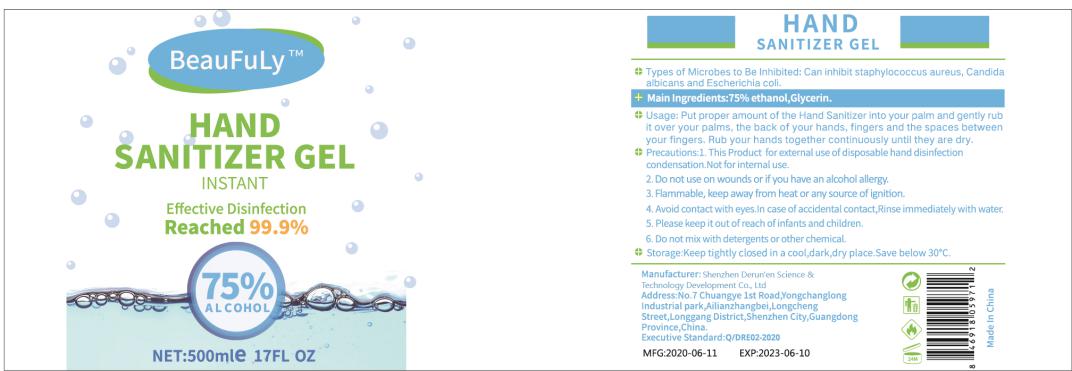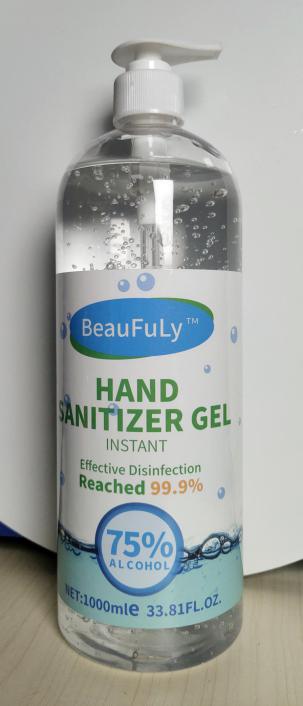 DRUG LABEL: HAND SANITIZER
NDC: 55029-002 | Form: GEL
Manufacturer: Shenzhen Derun'en Science & Technology Development Co., Ltd
Category: otc | Type: HUMAN OTC DRUG LABEL
Date: 20201121

ACTIVE INGREDIENTS: GLYCERIN 1 mg/100 mL; ALCOHOL 75 mL/100 mL
INACTIVE INGREDIENTS: CARBOMER COPOLYMER TYPE A

HAND SANITIZER

Active Ingredient(s)

Absolute ethanol Alcohol 75% v/v. glycerin 1%......Purpose: Antiseptic

Purpose

Antiseptic, Hand Sanitizer

Use

Hand Sanitizer to help reduce bacteria that potentially can cause disease. For use when soap and water are not available.

Warnings

For external use only. Flammable. Keep away from heat or flame

Do not use

- in children less than 2 months of age
- on open skin wounds

When using this product keep out of eyes, ears, and mouth. In case of contact with eyes, rinse eyes thoroughly with water.
Stop use and ask a doctor if irritation or rash occurs. These may be signs of a serious condition.
Keep out of reach of children. If swallowed, get medical help or contact a Poison Control Center right away.

Stop use and ask a doctor if irritation or rash occurs. These may be signs of a serious condition.

Keep out of reach of children. If swallowed, get medical help or contact a Poison Control Center right away.

Directions

- Put proper amount of the hand sanitizer into your palm and gently rub it over your palms, the back of your hands, fingers and the spaces between your fingers. Rub your hands together continuously until they are dry.
- Supervise children under 6 years of age when using this product to avoid swallowing.

Other information

Keep tightly closed in a cool, dark, dry place. Save below 30℃.

Inactive ingredients

Carbomer

Package Label - Principal Display Panel

500ML IN 1 BOTTLE NDC:55029-002-01

1000ML IN 1 BOTTLE NDC:55029-002-02